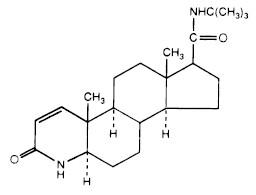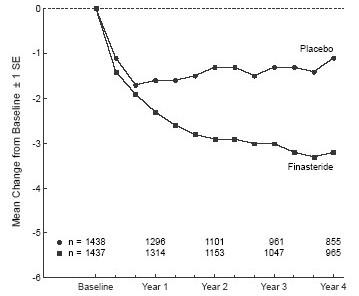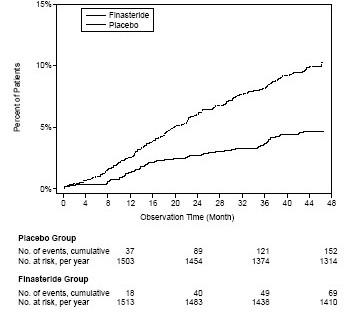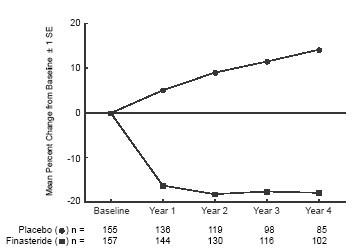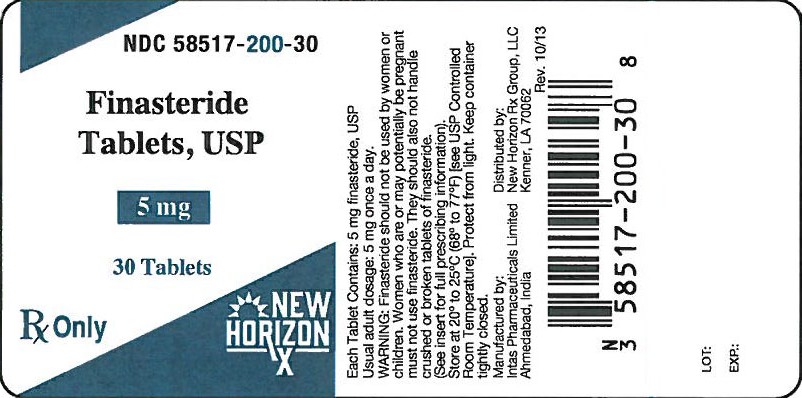 DRUG LABEL: Finasteride
NDC: 58517-200 | Form: TABLET, FILM COATED
Manufacturer: New Horizon Rx Group, LLC
Category: prescription | Type: HUMAN PRESCRIPTION DRUG LABEL
Date: 20131231

ACTIVE INGREDIENTS: FINASTERIDE 5 mg/1 1
INACTIVE INGREDIENTS: CELLULOSE, MICROCRYSTALLINE; LACTOSE MONOHYDRATE; STARCH, CORN; SODIUM STARCH GLYCOLATE TYPE A POTATO; HYPROMELLOSES; TITANIUM DIOXIDE; MAGNESIUM STEARATE; FD&C BLUE NO. 2; POLYETHYLENE GLYCOLS

FINASTERIDE TABLETS

Rx Only

DESCRIPTION

Finasteride, a synthetic 4-azasteroid compound, is a specific inhibitor of steroid Type II 5α-reductase, an intracellular enzyme that converts the androgen testosterone into 5α-dihydrotestosterone (DHT).

Finasteride is 4-azaandrost-1-ene-17-carboxamide, N-(1,1-dimethylethyl)-3-oxo-,(5α,17ß)-.The empirical formula of finasteride is C23H36N2O2 and its molecular weight is 372.55. Its structural formula is:

Finasteride is a white crystalline powder with a melting point near 250°C. It is freely soluble in chloroform and in lower alcohol solvents, but is practically insoluble in water.

Finasteride tablets USP for oral administration are film-coated tablets that contain 5 mg of finasteride and the following inactive ingredients: lactose monohydrate, microcrystalline cellulose, pregelatinized starch, sodium starch glycolate, hypromellose, titanium dioxide, magnesium stearate, lauryl macrogolglycerides, FD&C Blue # 2 aluminum lake and polyethylene glycol.

CLINICAL PHARMACOLOGY

The development and enlargement of the prostate gland is dependent on the potent androgen, 5α-dihydrotestosterone (DHT). Type II 5α-reductase metabolizes testosterone to DHT in the prostate gland, liver and skin. DHT induces androgenic effects by binding to androgen receptors in the cell nuclei of these organs.

Finasteride is a competitive and specific inhibitor of Type II 5α-reductase with which it slowly forms a stable enzyme complex. Turnover from this complex is extremely slow (t½ ~ 30 days). This has been demonstrated both in vivo and in vitro. Finasteride has no affinity for the androgen receptor. In man, the 5α-reduced steroid metabolites in blood and urine are decreased after administration of finasteride.

In man, a single 5 mg oral dose of finasteride produces a rapid reduction in serum DHT concentration, with the maximum effect observed 8 hours after the first dose. The suppression of DHT is maintained throughout the 24-hour dosing interval and with continued treatment. Daily dosing of finasteride at 5 mg/day for up to 4 years has been shown to reduce the serum DHT concentration by approximately 70%. The median circulating level of testosterone increased by approximately 10 to 20% but remained within the physiologic range.

Adult males with genetically inherited Type II 5α-reductase deficiency also have decreased levels of DHT. Except for the associated urogenital defects present at birth, no other clinical abnormalities related to Type II 5α-reductase deficiency have been observed in these individuals. These individuals have a small prostate gland throughout life and do not develop BPH.

In patients with BPH treated with finasteride (1 to 100 mg/day) for 7 to 10 days prior to prostatectomy, an approximate 80% lower DHT content was measured in prostatic tissue removed at surgery, compared to placebo; testosterone tissue concentration was increased up to 10 times over pretreatment levels, relative to placebo. Intraprostatic content of prostate-specific antigen (PSA) was also decreased.

In healthy male volunteers treated with finasteride for 14 days, discontinuation of therapy resulted in a return of DHT levels to pretreatment levels in approximately 2 weeks. In patients treated for three months, prostate volume, which declined by approximately 20%, returned to close to baseline value after approximately three months of discontinuation of therapy.

Pharmacokinetics

Absorption

In a study of 15 healthy young subjects, the mean bioavailability of finasteride 5 mg tablets was 63% (range 34 to 108%), based on the ratio of area under the curve (AUC) relative to an intravenous (IV) reference dose. Maximum finasteride plasma concentration averaged 37 ng/mL (range, 27 to 49 ng/mL) and was reached 1 to 2 hours postdose. Bioavailability of finasteride was not affected by food.

Distribution

Mean steady-state volume of distribution was 76 liters (range, 44 to 96 liters). Approximately 90% of circulating finasteride is bound to plasma proteins. There is a slow accumulation phase for finasteride after multiple dosing. After dosing with 5 mg/day of finasteride for 17 days, plasma concentrations of finasteride were 47 and 54% higher than after the first dose in men 45 to 60 years old (n=12) and ≥70 years old (n=12), respectively. Mean trough concentrations after 17 days of dosing were 6.2 ng/mL (range, 2.4 to 9.8 ng/mL) and 8.1 ng/mL (range, 1.8 to 19.7 ng/mL), respectively, in the two age groups. Although steady state was not reached in this study, mean trough plasma concentration in another study in patients with BPH (mean age, 65 years) receiving 5 mg/day was 9.4 ng/mL (range, 7.1 to 13.3 ng/mL; n=22) after over a year of dosing.

Finasteride has been shown to cross the blood brain barrier but does not appear to distribute preferentially to the CSF.

In 2 studies of healthy subjects (n=69) receiving finasteride 5 mg/day for 6 to 24 weeks, finasteride concentrations in semen ranged from undetectable (<0.1 ng/mL) to 10.54 ng/mL. In an earlier study using a less sensitive assay, finasteride concentrations in the semen of 16 subjects receiving finasteride 5 mg/day ranged from undetectable (<1.0 ng/mL) to 21 ng/mL. Thus, based on a 5 mL ejaculate volume, the amount of finasteride in semen was estimated to be 50- to 100-fold less than the dose of finasteride (5 mcg) that had no effect on circulating DHT levels in men (see also PRECAUTIONS, Pregnancy).

Metabolism

Finasteride is extensively metabolized in the liver, primarily via the cytochrome P450 3A4 enzyme subfamily. Two metabolites, the t-butyl side chain monohydroxylated and monocarboxylic acid metabolites, have been identified that possess no more than 20% of the 5α-reductase inhibitory activity of finasteride.

Excretion

In healthy young subjects (n=15), mean plasma clearance of finasteride was 165 mL/min (range, 70 to 279 mL/min) and mean elimination half-life in plasma was 6 hours (range, 3 to 16 hours). Following an oral dose of 14C-finasteride in man (n=6), a mean of 39% (range, 32 to 46%) of the dose was excreted in the urine in the form of metabolites; 57% (range, 51 to 64%) was excreted in the feces.

The mean terminal half-life of finasteride in subjects ≥70 years of age was approximately 8 hours (range, 6 to 15 hours; n=12), compared with 6 hours (range, 4 to 12 hours; n=12) in subjects 45 to 60 years of age. As a result, mean AUC(0 to 24 hr) after 17 days of dosing was 15% higher in subjects ≥70 years of age than in subjects 45 to 60 years of age (p=0.02).

Special Populations

Pediatric: Finasteride pharmacokinetics have not been investigated in patients <18 years of age.

Gender: Finasteride pharmacokinetics in women are not available.

Geriatric: No dosage adjustment is necessary in the elderly. Although the elimination rate of finasteride is decreased in the elderly, these findings are of no clinical significance. See also Pharmacokinetics, Excretion, PRECAUTIONS, Geriatric Use and DOSAGE AND ADMINISTRATION.

Race: The effect of race on finasteride pharmacokinetics has not been studied.

Renal Insufficiency: No dosage adjustment is necessary in patients with renal insufficiency. In patients with chronic renal impairment, with creatinine clearances ranging from 9.0 to 55 mL/min, AUC, maximum plasma concentration, half-life, and protein binding after a single dose of 14C-finasteride were similar to values obtained in healthy volunteers. Urinary excretion of metabolites was decreased in patients with renal impairment. This decrease was associated with an increase in fecal excretion of metabolites. Plasma concentrations of metabolites were significantly higher in patients with renal impairment (based on a 60% increase in total radioactivity AUC). However, finasteride has been well tolerated in BPH patients with normal renal function receiving up to 80 mg/day for 12 weeks, where exposure of these patients to metabolites would presumably be much greater.

Hepatic Insufficiency: The effect of hepatic insufficiency on finasteride pharmacokinetics has not been studied. Caution should be used in the administration of finasteride in those patients with liver function abnormalities, as finasteride is metabolized extensively in the liver.

Drug Interactions

(also see PRECAUTIONS, Drug Interactions)

No drug interactions of clinical importance have been identified. Finasteride does not appear to affect the cytochrome P450-linked drug metabolism enzyme system. Compounds that have been tested in man have included antipyrine, digoxin, propranolol, theophylline, and warfarin, and no clinically meaningful interactions were found.

Mean (SD) Pharmacokinetic Parameters in Healthy Young Subjects (n=15)
 | Mean (±SD)
Bioavailability | 63% (34 to 108%)*
Clearance (mL/min) | 165 (55)
Volume of Distribution (L) | 76 (14)
Half-Life (hours) | 6.2 (2.1)
*Range

Mean (SD) Noncompartmental Pharmacokinetic Parameters After Multiple Doses of 5 mg/day in Older Men
 | Mean (± SD)
 | 45 to 60 years old (n=12) | ≥70 years old (n=12)
AUC (ng·hr/mL) | 389 (98) | 463 (186)
Peak Concentration (ng/mL) | 46.2 (8.7) | 48.4 (14.7)
Time to Peak (hours) | 1.8 (0.7) | 1.8 (0.6)
Half-Life (hours)* | 6.0 (1.5) | 8.2 (2.5)
* First-dose values; all other parameters are last-dose values

CLINICAL STUDIES

Finasteride 5 mg/day was initially evaluated in patients with symptoms of BPH and enlarged prostates by digital rectal examination in two 1-year, placebo-controlled, randomized, double-blind studies and their 5-year open extensions.

Finasteride was further evaluated in a long-term efficacy and safety study, a double-blind, randomized, placebo-controlled, 4-year, multicenter study. 3040 patients between the ages of 45 and 78, with moderate to severe symptoms of BPH and an enlarged prostate upon digital rectal examination, were randomized into the study (1524 to finasteride, 1516 to placebo) and 3016 patients were evaluable for efficacy. 1883 patients completed the 4-year study (1000 in the finasteride group, 883 in the placebo group).

Effect on Symptom Score

Symptoms were quantified using a score similar to the American Urological Association Symptom Score, which evaluated both obstructive symptoms (impairment of size and force of stream, sensation of incomplete bladder emptying, delayed or interrupted urination) and irritative symptoms (nocturia, daytime frequency, need to strain or push the flow of urine) by rating on a 0 to 5 scale for six symptoms and a 0 to 4 scale for one symptom, for a total possible score of 34.

Patients in a long-term efficacy and safety study had moderate to severe symptoms at baseline (mean of approximately 15 points on a 0 to 34 point scale). Patients randomized to finasteride who remained on therapy for 4 years had a mean (± 1 SD) decrease in symptom score of 3.3 (± 5.8) points compared with 1.3 (± 5.6) points in the placebo group. (See Figure 1.) A statistically significant improvement in symptom score was evident at 1 year in patients treated with finasteride vs placebo (–2.3 vs –1.6), and this improvement continued through Year 4.

Figure 1: Symptom Score in a long-term efficacy and safety study

Results seen in earlier studies were comparable to those seen in a long-term efficacy and safety study. Although an early improvement in urinary symptoms was seen in some patients, a therapeutic trial of at least 6 months was generally necessary to assess whether a beneficial response in symptom relief had been achieved. The improvement in BPH symptoms was seen during the first year and maintained throughout an additional 5 years of open extension studies.

Effect on the Need for Surgery

In a long-term efficacy and safety study, efficacy was also assessed by evaluating treatment failures. Treatment failure was prospectively defined as BPH-related urological events or clinical deterioration, lack of improvement and/or the need for alternative therapy. BPH-related urological events were defined as urological surgical intervention. Complete event information was available for 92% of the patients. The following table (Table 1) summarizes the results.

Table 1: All Treatment Failures in a long-term efficacy and safety study
 | Patients (%)*
Event | Placebo N=1503 | Finasteride N=1513 | Relative Risk† | 95% CI | P Value†
All Treatment Failures | 37.1 | 26.2 | 0.68 | (0.57 to 0.79) | <0.001
Surgical Interventions for BPH | 10.1 | 4.6 | 0.45 | (0.32 to 0.63) | <0.001
Two consecutive symptom scores ≥20 | 9.2 | 6.7
Bladder Stone | 0.4 | 0.5
Incontinence | 2.1 | 1.7
Renal Failure | 0.5 | 0.6
UTI | 5.7 | 4.9
Discontinuation due to worsening of BPH, lack of improvement, or to receive other medical treatment | 21.8 | 13.3
*patients with multiple events may be counted more than once for each type of event
†Hazard ratio based on log rank test

Compared with placebo, finasteride was associated with a significantly lower need for BPH-related surgery [13.2% for placebo vs 6.6% for finasteride; 51% reduction in risk, 95% CI: (34 to 63%)]. Compared with placebo, finasteride was associated with a significantly lower risk for surgery [10.1% for placebo vs 4.6% for finasteride; 55% reduction in risk, 95% CI: (37 to 68%)]; see Figure 2.

Figure 2 Percent of Patients Having Surgery for BPH, Including TURP

Effect on Maximum Urinary Flow Rate

In the patients in a long-term efficacy and safety study who remained on therapy for the duration of the study and had evaluable urinary flow data, finasteride increased maximum urinary flow rate by 1.9 mL/sec compared with 0.2 mL/sec in the placebo group.

There was a clear difference between treatment groups in maximum urinary flow rate in favor of finasteride by month 4 (1.0 vs 0.3 mL/sec) which was maintained throughout the study. In the earlier 1-year studies, increase in maximum urinary flow rate was comparable to a long-term efficacy and safety study and was maintained through the first year and throughout an additional 5 years of open extension studies.

Effect on Prostate Volume

In a long-term efficacy and safety study, prostate volume was assessed yearly by magnetic resonance imaging (MRI) in a subset of patients. In patients treated with finasteride who remained on therapy, prostate volume was reduced compared with both baseline and placebo throughout the 4-year study. Finasteride decreased prostate volume by 17.9% (from 55.9 mL at baseline to 45.8 mL at 4 years) compared with an increase of 14.1% (from 51.3 mL to 58.5 mL) in the placebo group (p<0.001). (See Figure 3.)

Results seen in earlier studies were comparable to those seen in a long-term efficacy and safety study. Mean prostate volume at baseline ranged between 40 to 50 mL. The reduction in prostate volume was seen during the first year and maintained throughout an additional five years of open extension studies.

Figure 3 Prostate Volume in a long-term efficacy and safety study

Prostate Volume as a Predictor of Therapeutic Response

A meta-analysis combining 1-year data from seven double-blind, placebo-controlled studies of similar design, including 4491 patients with symptomatic BPH, demonstrated that, in patients treated with finasteride , the magnitude of symptom response and degree of improvement in maximum urinary flow rate were greater in patients with an enlarged prostate at baseline.

Summary of Clinical Studies

The data from these studies, showing improvement in BPH-related symptoms, reduction in treatment failure (BPH-related urological events), increased maximum urinary flow rates, and decreasing prostate volume, suggest that finasteride arrests the disease process of BPH in men with an enlarged prostate.

INDICATIONS AND USAGE

Finasteride tablets USP, 5 mg is indicated for the treatment of symptomatic benign prostatic hyperplasia (BPH) in men with an enlarged prostate to:

- Improve symptoms
- Reduce the risk of the need for surgery including transurethral resection of the prostate (TURP) and prostatectomy.

CONTRAINDICATIONS

Finasteride is contraindicated in the following:

Hypersensitivity to any component of this medication.

Pregnancy. Finasteride use is contraindicated in women when they are or may potentially be pregnant. Because of the ability of Type II 5α-reductase inhibitors to inhibit the conversion of testosterone to DHT, finasteride may cause abnormalities of the external genitalia of a male fetus of a pregnant woman who receives finasteride. If this drug is used during pregnancy, or if pregnancy occurs while taking this drug, the pregnant woman should be apprised of the potential hazard to the male fetus. (See also WARNINGS, EXPOSURE OF WOMEN —RISK TO MALE FETUS and PRECAUTIONS, Information for Patients and Pregnancy.) In female rats, low doses of finasteride administered during pregnancy have produced abnormalities of the external genitalia in male offspring.

WARNINGS

Finasteride is not indicated for use in pediatric patients (see PRECAUTIONS, Pediatric Use) or women (see also WARNINGS, EXPOSURE OF WOMEN — RISK TO MALE FETUS; PRECAUTIONS, Information for Patients and Pregnancy; and HOW SUPPLIED).

EXPOSURE OF WOMEN — RISK TO MALE FETUS

Women should not handle crushed or broken finasteride tablets USP, 5 mg when they are pregnant or may potentially be pregnant because of the possibility of absorption of finasteride and the subsequent potential risk to a male fetus. Finasteride tablets USP, 5 mg are coated and will prevent contact with the active ingredient during normal handling, provided that the tablets have not been broken or crushed. (See CONTRAINDICATIONS; PRECAUTIONS, Information for Patients and Pregnancy; and HOW SUPPLIED.)

PRECAUTIONS

General

Prior to initiating therapy with finasteride, appropriate evaluation should be performed to identify other conditions such as infection, prostate cancer, stricture disease, hypotonic bladder or other neurogenic disorders that might mimic BPH.

Patients with large residual urinary volume and/or severely diminished urinary flow should be carefully monitored for obstructive uropathy. These patients may not be candidates for finasteride therapy.

Caution should be used in the administration of finasteride in those patients with liver function abnormalities, as finasteride is metabolized extensively in the liver.

Effects on PSA and Prostate Cancer Detection

No clinical benefit has been demonstrated in patients with prostate cancer treated with finasteride. Patients with BPH and elevated PSA were monitored in controlled clinical studies with serial PSAs and prostate biopsies. In these BPH studies, finasteride did not appear to alter the rate of prostate cancer detection, and the overall incidence of prostate cancer was not significantly different in patients treated with finasteride or placebo.

Finasteride causes a decrease in serum PSA levels by approximately 50% in patients with BPH. This decrease is predictable over the entire range of PSA values, although it may vary in individual patients. Analysis of PSA data from over 3000 patients in a long-term efficacy and safety study confirmed that in typical patients treated with finasteride for six months or more, PSA values should be doubled for comparison with normal ranges in untreated men. This adjustment preserves the sensitivity and specificity of the PSA assay and maintains its ability to detect prostate cancer. Finasteride may also cause decreases in serum PSA in the presence of prostate cancer.

Any confirmed increases in PSA levels from nadir while on finasteride may signal the presence of prostate cancer and should be carefully evaluated, even if those values are still within the normal range for men not taking a 5α-reductase inhibitor. Non-compliance with finasteride therapy may also affect PSA test results.

Percent free PSA (free to total PSA ratio) is not significantly decreased by finasteride. The ratio of free to total PSA remains constant even under the influence of finasteride. If clinicians elect to use percent free PSA as an aid in the detection of prostate cancer in men undergoing finasteride therapy, no adjustment to its value appears necessary.

Information for Patients

Women should not handle crushed or broken finasteride tablets USP, 5 mg when they are pregnant or may potentially be pregnant because of the possibility of absorption of finasteride and the subsequent potential risk to the male fetus (see CONTRAINDICATIONS; WARNINGS, EXPOSURE OF WOMEN — RISK TO MALE FETUS; PRECAUTIONS, Pregnancy and HOW SUPPLIED).

Physicians should inform patients that the volume of ejaculate may be decreased in some patients during treatment with finasteride. This decrease does not appear to interfere with normal sexual function. However, impotence and decreased libido may occur in patients treated with finasteride (see ADVERSE REACTIONS).

Physicians should instruct their patients to promptly report any changes in their breasts such as lumps, pain or nipple discharge. Breast changes including breast enlargement, tenderness and neoplasm have been reported (see ADVERSE REACTIONS).

Physicians should instruct their patients to read the patient package insert before starting therapy with finasteride and to reread it each time the prescription is renewed so that they are aware of current information for patients regarding finasteride.

Drug/Laboratory Test Interactions

In patients with BPH, finasteride has no effect on circulating levels of cortisol, estradiol, prolactin, thyroid-stimulating hormone, or thyroxine. No clinically meaningful effect was observed on the plasma lipid profile (i.e., total cholesterol, low density lipoproteins, high density lipoproteins and triglycerides) or bone mineral density. Increases of about 10% were observed in luteinizing hormone (LH) and follicle-stimulating hormone (FSH) in patients receiving finasteride, but levels remained within the normal range. In healthy volunteers, treatment with finasteride did not alter the response of LH and FSH to gonadotropin-releasing hormone indicating that the hypothalamic-pituitary-testicular axis was not affected.

Treatment with finasteride for 24 weeks to evaluate semen parameters in healthy male volunteers revealed no clinically meaningful effects on sperm concentration, mobility, morphology, or pH. A 0.6 mL (22.1%) median decrease in ejaculate volume with a concomitant reduction in total sperm per ejaculate was observed. These parameters remained within the normal range and were reversible upon discontinuation of therapy with an average time to return to baseline of 84 weeks.

Drug Interactions

No drug interactions of clinical importance have been identified. Finasteride does not appear to affect the cytochrome P450-linked drug metabolizing enzyme system. Compounds that have been tested in man have included antipyrine, digoxin, propranolol, theophylline, and warfarin and no clinically meaningful interactions were found.

Other Concomitant Therapy: Although specific interaction studies were not performed, finasteride was concomitantly used in clinical studies with acetaminophen, acetylsalicylic acid, α-blockers, angiotensin-converting enzyme (ACE) inhibitors, analgesics, anti-convulsants, beta-adrenergic blocking agents, diuretics, calcium channel blockers, cardiac nitrates, HMG-CoA reductase inhibitors, nonsteroidal anti-inflammatory drugs (NSAIDs), benzodiazepines, H2 antagonists and quinolone anti-infectives without evidence of clinically significant adverse interactions.

Carcinogenesis, Mutagenesis, Impairment of Fertility

No evidence of a tumorigenic effect was observed in a 24-month study in Sprague-Dawley rats receiving doses of finasteride up to 160 mg/kg/day in males and 320 mg/kg/day in females. These doses produced respective systemic exposure in rats of 111 and 274 times those observed in man receiving the recommended human dose of 5 mg/day. All exposure calculations were based on calculated AUC(0 to 24 hr) for animals and mean AUC(0 to 24 hr) for man (0.4 mcg•hr/mL).

In a 19-month carcinogenicity study in CD-1 mice, a statistically significant (p≤0.05) increase in the incidence of testicular Leydig cell adenomas was observed at a dose of 250 mg/kg/day (228 times the human exposure). In mice at a dose of 25 mg/kg/day (23 times the human exposure, estimated) and in rats at a dose of ≥40 mg/kg/day (39 times the human exposure) an increase in the incidence of Leydig cell hyperplasia was observed. A positive correlation between the proliferative changes in the Leydig cells and an increase in serum LH levels (2- to 3-fold above control) has been demonstrated in both rodent species treated with high doses of finasteride. No drug-related Leydig cell changes were seen in either rats or dogs treated with finasteride for 1 year at doses of 20 mg/kg/day and 45 mg/kg/day (30 and 350 times, respectively, the human exposure) or in mice treated for 19 months at a dose of 2.5 mg/kg/day (2.3 times the human exposure, estimated).

No evidence of mutagenicity was observed in an invitro bacterial mutagenesis assay, a mammalian cell mutagenesis assay, or in an in vitro alkaline elution assay. In an invitro chromosome aberration assay, using Chinese hamster ovary cells, there was a slight increase in chromosome aberrations. These concentrations correspond to 4000 to 5000 times the peak plasma levels in man given a total dose of 5 mg. In an invivo chromosome aberration assay in mice, no treatment-related increase in chromosome aberration was observed with finasteride at the maximum tolerated dose of 250 mg/kg/day (228 times the human exposure) as determined in the carcinogenicity studies.

In sexually mature male rabbits treated with finasteride at 80 mg/kg/day (543 times the human exposure) for up to 12 weeks, no effect on fertility, sperm count, or ejaculate volume was seen. In sexually mature male rats treated with 80 mg/kg/day of finasteride (61 times the human exposure), there were no significant effects on fertility after 6 or 12 weeks of treatment; however, when treatment was continued for up to 24 or 30 weeks, there was an apparent decrease in fertility, fecundity and an associated significant decrease in the weights of the seminal vesicles and prostate. All these effects were reversible within 6 weeks of discontinuation of treatment. No drug-related effect on testes or on mating performance has been seen in rats or rabbits. This decrease in fertility in finasteride-treated rats is secondary to its effect on accessory sex organs (prostate and seminal vesicles) resulting in failure to form a seminal plug. The seminal plug is essential for normal fertility in rats and is not relevant in man.

Pregnancy

Pregnancy Category X

See CONTRAINDICATIONS.

Finasteride is not indicated for use in women.

Administration of finasteride to pregnant rats at doses ranging from 100 mcg/kg/day to 100 mg/kg/day (1 to 1000 times the recommended human dose of 5 mg/day) resulted in dose-dependent development of hypospadias in 3.6 to 100% of male offspring. Pregnant rats produced male offspring with decreased prostatic and seminal vesicular weights, delayed preputial separation and transient nipple development when given finasteride at ≥30 mcg/kg/day (≥3/10 of the recommended human dose of 5 mg/day) and decreased anogenital distance when given finasteride at ≥3 mcg/kg/day (≥3/100 of the recommended human dose of 5 mg/day). The critical period during which these effects can be induced in male rats has been defined to be days 16 to 17 of gestation. The changes described above are expected pharmacological effects of drugs belonging to the class of Type II 5α-reductase inhibitors and are similar to those reported in male infants with a genetic deficiency of Type II 5α-reductase. No abnormalities were observed in female offspring exposed to any dose of finasteride in utero.

No developmental abnormalities have been observed in first filial generation (F1) male or female offspring resulting from mating finasteride-treated male rats (80 mg/kg/day; 61 times the human exposure) with untreated females. Administration of finasteride at 3 mg/kg/day (30 times the recommended human dose of 5 mg/day) during the late gestation and lactation period resulted in slightly decreased fertility in F1 male offspring. No effects were seen in female offspring. No evidence of malformations has been observed in rabbit fetuses exposed to finasteride in utero from days 6 to 18 of gestation at doses up to 100 mg/kg/day (1000 times the recommended human dose of 5 mg/day). However, effects on male genitalia would not be expected since the rabbits were not exposed during the critical period of genital system development.

The in utero effects of finasteride exposure during the period of embryonic and fetal development were evaluated in the rhesus monkey (gestation days 20 to 100), a species more predictive of human development than rats or rabbits. Intravenous administration of finasteride to pregnant monkeys at doses as high as 800 ng/day (at least 60 to 120 times the highest estimated exposure of pregnant women to finasteride from semen of men taking 5 mg/day) resulted in no abnormalities in male fetuses. In confirmation of the relevance of the rhesus model for human fetal development, oral administration of a dose of finasteride (2 mg/kg/day; 20 times the recommended human dose of 5 mg/day or approximately 1 to 2 million times the highest estimated exposure to finasteride from semen of men taking 5 mg/day) to pregnant monkeys resulted in external genital abnormalities in male fetuses. No other abnormalities were observed in male fetuses and no finasteride-related abnormalities were observed in female fetuses at any dose.

Nursing Mothers

Finasteride is not indicated for use in women.

It is not known whether finasteride is excreted in human milk.

Pediatric Use

Finasteride is not indicated for use in pediatric patients.

Safety and effectiveness in pediatric patients have not been established.

Geriatric Use

Of the total number of subjects included in a long-term efficacy and safety study, 1480 and 105 subjects were 65 and over and 75 and over, respectively. No overall differences in safety or effectiveness were observed between these subjects and younger subjects, and other reported clinical experience has not identified differences in responses between the elderly and younger patients. No dosage adjustment is necessary in the elderly (see CLINICAL PHARMACOLOGY, Pharmacokinetics and Clinical Studies).

ADVERSE REACTIONS

Finasteride is generally well tolerated; adverse reactions usually have been mild and transient.

4-Year Placebo-Controlled Study

In a long-term efficacy and safety study, 1524 patients treated with finasteride and 1516 patients treated with placebo were evaluated for safety over a period of 4 years. The most frequently reported adverse reactions were related to sexual function. 3.7% (57 patients) treated with finasteride and 2.1% (32 patients) treated with placebo discontinued therapy as a result of adverse reactions related to sexual function, which are the most frequently reported adverse reactions.

Table 2 presents the only clinical adverse reactions considered possibly, probably or definitely drug related by the investigator, for which the incidence on finasteride was ≥1% and greater than placebo over the 4 years of the study. In years 2 to 4 of the study, there was no significant difference between treatment groups in the incidences of impotence, decreased libido and ejaculation disorder.

TABLE 2 Drug-Related Adverse Experiences
 | Year 1 (%) |  | Years 2, 3 and 4* (%)
 | Finasteride | Placebo | Finasteride | Placebo
Impotence | 8.1 | 3.7 | 5.1 | 5.1
Decreased Libido | 6.4 | 3.4 | 2.6 | 2.6
Decreased Volume of Ejaculate | 3.7 | 0.8 | 1.5 | 0.5
Ejaculation Disorder | 0.8 | 0.1 | 0.2 | 0.1
Breast Enlargement | 0.5 | 0.1 | 1.8 | 1.1
Breast Tenderness | 0.4 | 0.1 | 0.7 | 0.3
Rash | 0.5 | 0.2 | 0.5 | 0.1
N = 1524 and 1516, finasteride vs placebo, respectively
*Combined Years 2 to 4

Phase III Studies and 5-Year Open Extensions

The adverse experience profile in the 1-year, placebo-controlled, Phase III studies, the 5-year open extensions, and a long-term efficacy and safety study were similar.

Long-Term Data

There is no evidence of increased adverse experiences with increased duration of treatment with finasteride. New reports of drug-related sexual adverse experiences decreased with duration of therapy.

During a 4- to 6-year placebo- and comparator-controlled study that enrolled 3047 men, there were 4 cases of breast cancer in men treated with finasteride but no cases in men not treated with finasteride. During the 4-year, placebo-controlled a long-term efficacy and safety study that enrolled 3040 men, there were 2 cases of breast cancer in placebo-treated men, but no cases were reported in men treated with finasteride. The relationship between long-term use of finasteride and male breast neoplasia is currently unknown.

In a 7-year placebo-controlled trial that enrolled 18,882 healthy men, 9060 had prostate needle biopsy data available for analysis. In the finasteride group, 280 (6.4%) men had prostate cancer with Gleason scores of 7 to 10 detected on needle biopsy vs. 237 (5.1%) men in the placebo group. Of the total cases of prostate cancer diagnosed in this study, approximately 98% were classified as intracapsular (stage T1 or T2). The clinical significance of these findings is unknown. This information from the literature (Thompson IM, Goodman PJ, Tangen CM, et al. The influence of finasteride on the development of prostate cancer. N Engl J Med 2003;349:213 to 22) is provided for consideration by physicians when finasteride is used as indicated (see INDICATIONS AND USAGE). Finasteride is not approved to reduce the risk of developing prostate cancer.

Post-Marketing Experience

The following additional adverse effects have been reported in post-marketing experience:

- hypersensitivity reactions, including pruritus, urticaria, and swelling of the lips and face
- testicular pain.
- male breast cancer.

OVERDOSAGE

Patients have received single doses of finasteride up to 400 mg and multiple doses of finasteride up to 80 mg/day for three months without adverse effects. Until further experience is obtained, no specific treatment for an overdose with finasteride can be recommended.

Significant lethality was observed in male and female mice at single oral doses of 1500 mg/m2 (500 mg/kg) and in female and male rats at single oral doses of 2360 mg/m2 (400 mg/kg) and 5900 mg/ m2 (1000 mg/kg), respectively.

DOSAGE AND ADMINISTRATION

The recommended dose is 5 mg orally once a day.

Finasteride tablets USP, 5 mg may be administered with or without meals.

No dosage adjustment is necessary for patients with renal impairment or for the elderly (see CLINICAL PHARMACOLOGY, Pharmacokinetics).

HOW SUPPLIED

Finasteride tablets USP, 5 mg: blue, 7 mm, round, biconvex, film coated tablets, marked ‘F5’ on one side and plain on other side.

They are supplied as follows:

NDC 58517-200-30 Bottles of 30

Storage and Handling

Store at 20° to 25°C (68° to 77°F) [See USP Controlled Room Temperature]. Protect from light and keep container tightly closed.

Women should not handle crushed or broken finasteride tablets USP, 5 mg when they are pregnant or may potentially be pregnant because of the possibility of absorption of finasteride and the subsequent potential risk to a male fetus (see WARNINGS, EXPOSURE OF WOMEN —RISK TO MALE FETUS, and PRECAUTIONS, Information for Patients and Pregnancy).

Distributed by:
New Horizon Rx Group, LLC
Kenner, LA 70062

Manufactured By:
Intas Pharmaceuticals Limited,
Plot No.: 457, 458,
Village – Matoda,
Bavla Road, Ta.- Sanand,
Dist.- Ahmedabad – 382 210,

INDIA.

10 6584 2 626710

Rev. 11/13

Patient Information about Finasteride Tablets USP, 5 mg
(fin-AS-tur-eyed)

Finasteride Tablets USP, 5 mg is for use by men only.

Please read this leaflet before you start taking finasteride tablets USP, 5 mg. Also, read it each time you renew your prescription, just in case anything has changed. Remember, this leaflet does not take the place of careful discussions with your doctor. You and your doctor should discuss finasteride tablets USP, 5 mg when you start taking your medication and at regular checkups.

What is finasteride tablets USP, 5 mg?
Finasteride tablets USP, 5 mg is a medication used to treat symptoms of benign prostatic hyperplasia (BPH) in men with an enlarged prostate. Finasteride may also be used to reduce the risk of a sudden inability to pass urine and the need for surgery related to BPH in men with an enlarged prostate.

Who should NOT take finasteride tablets USP, 5 mg?
Finasteride Tablets USP, 5 mg is for use by MEN only.

Do Not Take finasteride tablets USP, 5 mg if you are:

- a woman who is pregnant or may potentially be pregnant. Finasteride may harm your unborn baby. Do not touch or handle crushed or broken finasteride tablets USP, 5 mg (see “A warning about finasteride and pregnancy”).
- allergic to finasteride or any of the ingredients in finasteride tablets USP, 5 mg. See the end of this leaflet for a complete list of ingredients in finasteride tablets USP, 5 mg.

A warning about finasteride and pregnancy.

Women who are or may potentially be pregnant must not use finasteride. They should also not handle crushed or broken finasteride tablets USP, 5 mg. Finasteride Tablets USP, 5 mg are coated and will prevent contact with the active ingredient during normal handling, provided that the tablets are not broken or crushed.

If a woman who is pregnant with a male baby absorbs the active ingredient in finasteride tablets USP, 5 mg after oral use or through the skin, it may cause the male baby to be born with abnormalities of the sex organs. If a woman who is pregnant comes into contact with the active ingredient in finasteride tablets USP, 5 mg, a doctor should be consulted.

How should I take finasteride tablets USP, 5 mg?

Follow your doctor's instruction.

- Take one tablet by mouth each day. To avoid forgetting to take finasteride tablets USP, 5 mg, you can take it at the same time every day.
- If you forget to take finasteride tablets USP, 5 mg, do not take an extra tablet. Just take the next tablet as usual.
- You may take finasteride tablets USP, 5 mg with or without food.
- Do not share finasteride tablets USP, 5 mg with anyone else; it was prescribed only for you.

What are the possible side effects of finasteride tablets USP, 5 mg?

The most common side effects of finasteride tablets USP, 5 mg include:

- trouble getting or keeping an erection (impotence)
- decrease in sex drive
- decreased volume of ejaculate
- ejaculation disorders
- enlarged or painful breast. You should promptly report to your doctor any changes in your breasts such as lumps, pain or nipple discharge.

In addition, the following have been reported in general use with finasteride tablets USP, 5 mg:

- allergic reactions, including rash, itching, hives, and swelling of the lips and face.
- rarely, some men may have testicular pain.
- in rare cases, male breast cancer has been reported.

You should discuss side effects with your doctor before taking finasteride tablets USP, 5 mg and anytime you think you are having a side effect. These are not all the possible side effects with finasteride tablets USP, 5 mg. For more information, ask your doctor or pharmacist.

Call your doctor for medical advice about side effects. You may report side effects to FDA at: 1-800-FDA-1088.

What you need to know while taking finasteride tablets USP, 5 mg

- You should see your doctor regularly while taking finasteride tablets USP, 5 mg. Follow your doctor's advice about when to have these checkups.
- Checking for prostate cancer. Your doctor has prescribed finasteride tablets USP, 5 mg for BPH and not for treatment of prostate cancer — but a man can have BPH and prostate cancer at the same time. Checking for prostate cancer should continue while you take finasteride tablets USP, 5 mg.
- About Prostate-Specific Antigen (PSA). Your doctor may have done a blood test called PSA for the screening of prostate cancer. Because finasteride tablets USP, 5 mg decreases PSA levels, you should tell your doctor(s) that you are taking finasteride tablets USP, 5 mg. Changes in PSA levels will need to be carefully evaluated by your doctor(s). Any increase in follow-up PSA levels from their lowest point should be carefully evaluated, even if the test results are still within the normal range. You should also tell your doctor if you have not been taking finasteride tablets USP, 5 mg as prescribed because this may affect the PSA test results. For more information, talk to your doctor.

How should I store finasteride tablets USP, 5 mg?

- Store finasteride tablets USP, 5 mg in a dry place at room temperature.
- Keep finasteride tablets USP, 5 mg in the original container and keep the container closed.

Finasteride Tablets USP, 5 mg are coated and will prevent contact with the active ingredient during normal handling, provided that the tablets are not broken or crushed.

Keep finasteride tablets USP, 5 mg and all medications out of the reach of children.

Do not give your finasteride tablets USP, 5 mg to anyone else. It has been prescribed only for you.

What are the ingredients in finasteride tablets USP, 5 mg?

Active ingredients: finasteride

Inactive ingredients: lactose monohydrate, microcrystalline cellulose, pregelatinized starch, sodium starch glycolate, hypromellose, titanium dioxide, magnesium stearate, lauryl macrogolglycerides, FD & C Blue # 2 aluminum lake and polyethylene glycol.

What is BPH?
BPH is an enlargement of the prostate gland. The prostate is located below the bladder. As the prostate enlarges, it may slowly restrict the flow of urine. This can lead to symptoms such as:

- a weak or interrupted urinary stream
- a feeling that you cannot empty your bladder completely
- a feeling of delay or hesitation when you start to urinate
- a need to urinate often, especially at night
- a feeling that you must urinate right away

In some men, BPH can lead to serious problems, including urinary tract infections, as well as the need for surgery.

What finasteride tablets USP, 5 mg does

Finasteride Tablets USP, 5 mg lowers levels of a hormone called DHT (dihydrotestosterone), which is a cause of prostate growth. Lowering DHT leads to shrinkage of the enlarged prostate gland in most men. This can lead to gradual improvement in urine flow and symptoms over the next several months. Finasteride Tablets USP, 5 mg will help reduce the risk of developing a sudden inability to pass urine and the need for surgery related to an enlarged prostate. However, since each case of BPH is different, you should know that:

- Even though the prostate shrinks, you may NOT notice an improvement in urine flow or symptoms.
- You may need to take finasteride tablets USP, 5 mg for six (6) months or more to see whether it improves your symptoms.
- Therapy with finasteride tablets USP, 5 mg may reduce your risk for a sudden inability to pass urine and the need for surgery for an enlarged prostate.

Distributed by:
New Horizon Rx Group, LLC
Kenner, LA 70062

Manufactured by:
Intas Pharmaceuticals Limited,
Plot No.: 457, 458,
Village – Matoda,
Bavla Road, Ta.- Sanand,
Dist.- Ahmedabad – 382 210,

INDIA.

10 6584 2 626710

Rev. 11/13